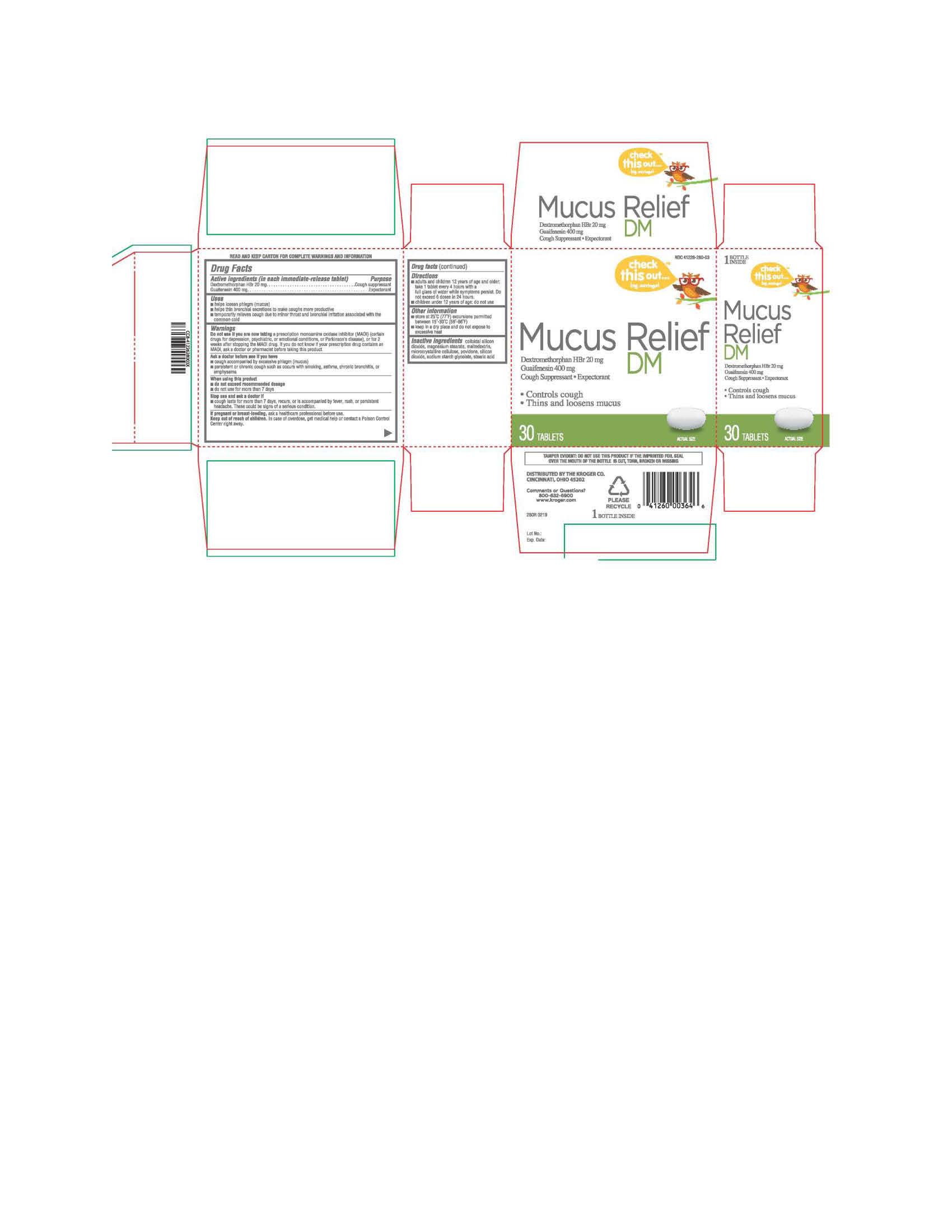 DRUG LABEL: MUCUS RELIEF DM
NDC: 41226-280 | Form: TABLET
Manufacturer: KROGER COMPANY
Category: otc | Type: HUMAN OTC DRUG LABEL
Date: 20190521

ACTIVE INGREDIENTS: DEXTROMETHORPHAN HYDROBROMIDE 20 mg/1 1; GUAIFENESIN 400 mg/1 1
INACTIVE INGREDIENTS: SODIUM STARCH GLYCOLATE TYPE A POTATO; MAGNESIUM STEARATE; MALTODEXTRIN; MICROCRYSTALLINE CELLULOSE; POVIDONE; STEARIC ACID; SILICON DIOXIDE

280R - KROGER MUCUS RELIEF DM

ACTIVE INGREDIENT

Each immediate-release tablet contains

Dextromethorphan HBr 20 mg Guaifenesin 400 mg

INACTIVE INGREDIENT

Colloidal Silicon Dioxide, Magnesium Stearate, Maltodextrin, Microcrystalline Cellulose, Povidone, Silicon Dioxide, Sodium Starch Glycolate, Stearic Acid

PURPOSE

Expectorant – Cough Suppressant

INDICATIONS AND USAGE

Helps loosen phlegm (mucus)

Helps thin bronchial secretions to make coughs more productive

Temporarily relieves cough due to minor throat and bronchial irritation associated with the common cold

DOSAGE AND ADMINISTRATION

Directions: Adults and children 12 years of age and older, take 1 tablet every 4 hours with a full glass of water while symptoms persist. Do not exceed 6 doses in 24 hours.

Children under 12 years of age do not use.

WARNINGS

WARNINGS: Do not use if you are now taking a prescription monoamine oxidase inhibitor (MAOI) (certain drugs for depression, psychiatric, or emotional conditions, or Parkinson’s disease), or for 2 weeks after stopping the MAOI drug. If you do not know if your prescription drug contains an MAOI, ask a doctor or pharmacist before taking this product.

Keep Out of Reach of Children: In case of overdose, get medical help or contact a Poison Control Center